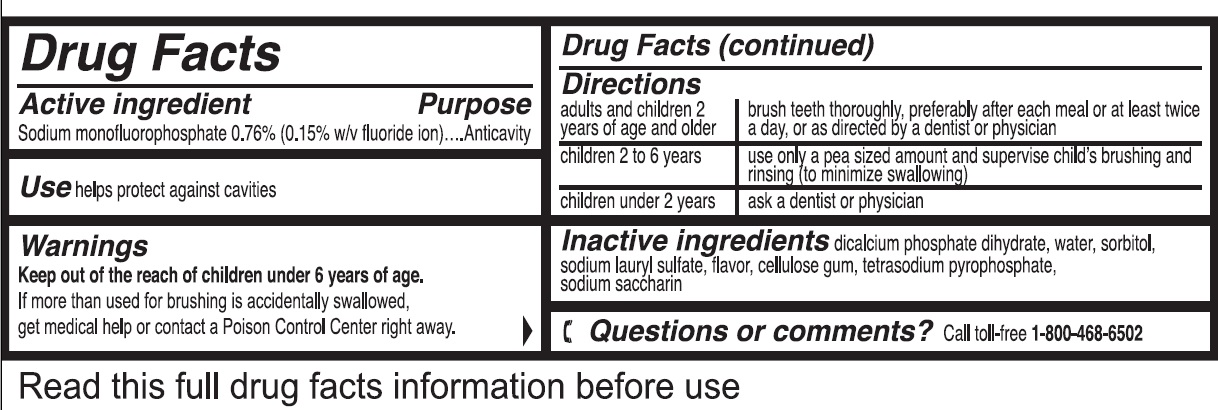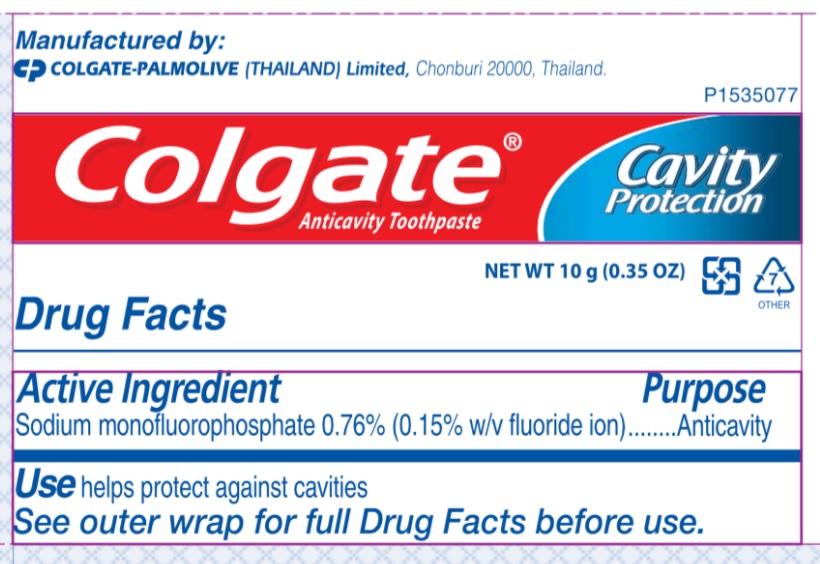 DRUG LABEL: Business Class Kit
NDC: 58701-002 | Form: PASTE, DENTIFRICE
Manufacturer: American Airlines, Inc.
Category: otc | Type: HUMAN OTC DRUG LABEL
Date: 20251209

ACTIVE INGREDIENTS: SODIUM MONOFLUOROPHOSPHATE 7.6 mg/1 g
INACTIVE INGREDIENTS: CALCIUM PHOSPHATE, DIBASIC, DIHYDRATE; WATER; SORBITOL; SODIUM LAURYL SULFATE; CARBOXYMETHYLCELLULOSE SODIUM; SODIUM PYROPHOSPHATE; SACCHARIN SODIUM; LIMONENE, (+/-)-

American Airlilne Business Class Kit

Active ingredient

Sodium monofluorophosphate 0.76% (0.15% w/v fluoride ion)

Purpose

Anticavity

Use

helps protect against cavities

Warnings

KEEP OUT OF REACH OF CHILDREN

If more than used for brushing is accidentally swallowed, get medical help or contact a Poison Control Center right away. Keep out of the reach of children under 6 years of age.

Directions

adults and children 2 years of age and older | brush teeth thoroughly, preferably after each meal or at least twice a day, or as directed by a dentist or physician
children 2 to 6 years | use only a pea sized amount and supervise child's brushing and rinsing (to minimize swallowing)
children under 2 years | ask a dentist or physician

Inactive ingredients

dicalcium phosphate dihydrate, water, sorbitol, sodium lauryl sulfate, flavor, cellulose gum, tetrasodium pyrophosphate, sodium saccharin

Questions or comments?

Call toll-free 1-800-468-6502